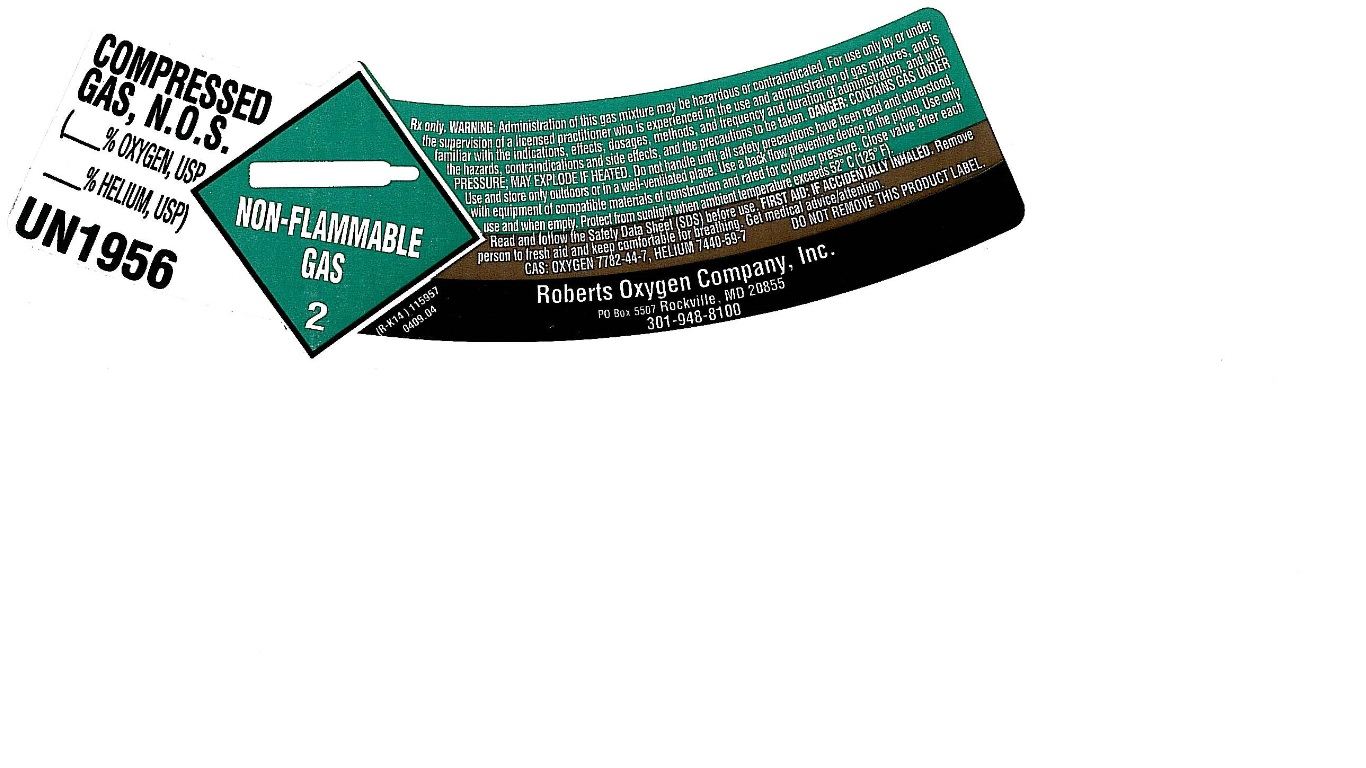 DRUG LABEL: Oxygen-Helium Mixture
NDC: 46123-510 | Form: GAS
Manufacturer: Roberts Oxygen Company, Inc.
Category: prescription | Type: HUMAN PRESCRIPTION DRUG LABEL
Date: 20251117

ACTIVE INGREDIENTS: OXYGEN 210 mL/1 L
INACTIVE INGREDIENTS: HELIUM

Oxygen - Helium Mixture -510

PACKAGE LABEL

COMPRESSED GAS, N.O.S (% OXYGEN, USP % HELIUM, USP)
UN1956
Rx only. WARNING: Administration of this gas mixture may be hazardous or contraindicated. For use only by or under the supervision of a licensed practitioner who is experienced in the use and administration of gas mixtures, and is familiar with the indications, effects, dosages, methods, and frequency and duration of administration, and with the hazards, contraindications and side effects, and the precautions to be taken. DANGER: CONTAINS GAS UNDER PRESSURE; MAY EXPLODE IF HEATED. Do not handle until all safety precautions have been read and understood. Use and store only outdoors or in a well-ventilated place. Use a back flow preventive device in the piping. Use only with equipment of compatible materials of construction and rated for cylinder pressure. Close valve after each use and when empty. Protect from sunlight when ambient temperature exceeds 52 C (125 F).
Read and follow the Safety Data Sheet (SDS) before use. FIRST AID: IF ACCIDENTALLY INHALED. Remov person to fresh aid and keep comfortable for breathing. Get medical advice/attention.
CAS: OXYGEN 7782-44-7, HELIUM 7440-59-7 DO NOT REMOVE THIS PRODUCT LABEL.
Roberts Oxygen Company, Inc.
PO Box 5507 Rockville, MD 20855
301-948-8100